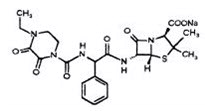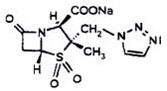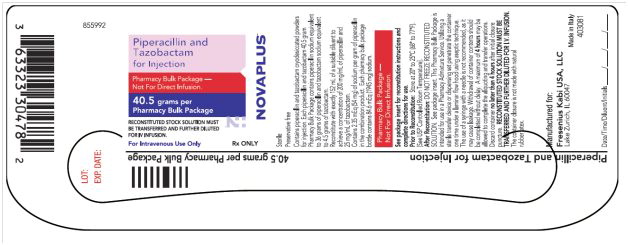 DRUG LABEL: Piperacillin and Tazobactam
NDC: 63323-304 | Form: INJECTION, POWDER, FOR SOLUTION
Manufacturer: Fresenius Kabi USA, LLC
Category: prescription | Type: HUMAN PRESCRIPTION DRUG LABEL
Date: 20241016

ACTIVE INGREDIENTS: PIPERACILLIN SODIUM 36 g/180 mL; TAZOBACTAM SODIUM 4.5 g/180 mL

HIGHLIGHTS OF PRESCRIBING INFORMATION

These highlights do not include all the information needed to use Piperacillin and Tazobactam for Injection safely and effectively. See full prescribing information for Piperacillin and Tazobactam for Injection.
Piperacillin and Tazobactam for Injection: pharmacy bulk package bottles
Initial U.S. Approval: 1993
To reduce the development of drug-resistant bacteria and maintain the effectiveness of Piperacillin and Tazobactam for Injection and other antibacterial drugs, Piperacillin and Tazobactam for Injection should be used only to treat infections that are proven or strongly suspected to be caused by bacteria.

1 INDICATIONS AND USAGE

Piperacillin and Tazobactam for Injection is a combination penicillin-class antibacterial and β-lactamase inhibitor indicated for treatment of:

- Intra-abdominal infections (1.1)
- Skin and skin structure infections (1.2)
- Female pelvic infections (1.3)
- Community-acquired pneumonia (1.4)
- Nosocomial pneumonia (1.5)

2 DOSAGE AND ADMINISTRATION

- The usual daily dose of Piperacillin and Tazobactam for Injection for adults is 3.375 g every six hours totaling 13.5 g (12.0 g piperacillin/1.5 g tazobactam) (2.1)
- Initial presumptive treatment of patients with nosocomial pneumonia should start with Piperacillin and Tazobactam for Injection at a dosage of 4.5 g every six hours plus an aminoglycoside, totaling 18.0 g (16.0 g piperacillin/2.0 g tazobactam). (2.2)
- Dosage in patients with renal impairment (≤40 mL/min of CRCL) and dialysis patients should be reduced, based on the degree of actual renal function impairment. (2.3)
- For children with appendicitis and/or peritonitis the recommended Piperacillin and Tazobactam for Injection dosage is 100 mg piperacillin/12.5 mg tazobactam per kilogram of body weight, every 8 hours in pediatric patients 9 months of age and older. For pediatric patients 2 to 9 months of age, the recommended dosage is 80 mg piperacillin/10 mg tazobactam per kilogram of body weight, every 8 hours. (2.4)
- Piperacillin and Tazobactam for Injection and aminoglycosides should be reconstituted, diluted, and administered separately. Co-administration via Y-site can be done under certain conditions. (2.6)

3 DOSAGE FORMS AND STRENGTHS

Piperacillin and Tazobactam for Injection: 40.5 g lyophilized powder for reconstitution in pharmacy bulk package bottles (3)

4 CONTRAINDICATIONS

Patients with a history of allergic reactions to any of the penicillins, cephalosporins, or β-lactamase inhibitors. (4)

5 WARNINGS AND PRECAUTIONS

- Serious hypersensitivity reactions (anaphylactic/anaphylactoid) reactions have been reported in patients receiving Piperacillin and Tazobactam for Injection. Discontinue Piperacillin and Tazobactam for Injection if a reaction occurs. (5.1)
- Serious skin reactions, such as Stevens-Johnson syndrome and toxic epidermal necrolysis, have been reported (5.2). Discontinue Piperacillin and Tazobactam for Injection for progressive rashes.
- Clostridium difficile associated diarrhea: evaluate patients if diarrhea occurs. (5.3)
- Hematological effects (including bleeding, leukopenia and neutropenia) have occurred. Monitor hematologic tests during prolonged therapy. (5.4)

6 ADVERSE REACTIONS

The most common adverse reactions (incidence >5%) are diarrhea, constipation, nausea, headache and insomnia. (6.1)

To report SUSPECTED ADVERSE REACTIONS, contact Fresenius Kabi USA, LLC Vigilance and Medical Affairs at 1-800-551-7176 or FDA at 1-800-FDA-1088 or www.fda.gov/medwatch.

7 DRUG INTERACTIONS

- Piperacillin and Tazobactam for Injection administration can significantly reduce tobramycin concentrations in hemodialysis patients. Monitor tobramycin concentrations in these patients. (7.1)
- Probenecid prolongs the half-lives of piperacillin and tazobactam and should not be co-administered with Piperacillin and Tazobactam for Injection unless the benefit outweighs the risk. (7.2)
- Monitor coagulation parameters in patients receiving Piperacillin and Tazobactam for Injection and heparin or oral anticoagulants. (7.3)
- Piperacillin and Tazobactam for Injection may prolong the neuromuscular blockade of vecuronium and other non-depolarizing muscle relaxants. Monitor for adverse reactions related to neuromuscular blockade. (7.4)

8 USE IN SPECIFIC POPULATIONS

Dosage in patients with renal impairment (≤40 mL/min of CRCL) should be reduced to the degree of actual renal function impairment. (2.3, 8.6)

FULL PRESCRIBING INFORMATION

BOXED WARNING

PHARMACY BULK PACKAGE – NOT FOR DIRECT INFUSION

Reconstituted stock solution must be transferred and further diluted for IV infusion

1 INDICATIONS AND USAGE

Piperacillin and tazobactam for injection is a combination product consisting of a penicillin-class antibacterial, piperacillin, and a β-lactamase inhibitor, tazobactam, indicated for the treatment of patients with moderate to severe infections caused by susceptible isolates of the designated bacteria in the conditions listed below.

1.1 Intra-abdominal Infections

Appendicitis (complicated by rupture or abscess) and peritonitis caused by β-lactamase producing isolates of Escherichia coli or the following members of the Bacteroides fragilis group: B. fragilis, B. ovatus, B. thetaiotaomicron, or B. vulgatus. The individual members of this group were studied in fewer than 10 cases.

1.2 Skin and Skin Structure Infections

Uncomplicated and complicated skin and skin structure infections, including cellulitis, cutaneous abscesses and ischemic/diabetic foot infections caused by β-lactamase producing isolates of Staphylococcus aureus.

1.3 Female Pelvic Infections

Postpartum endometritis or pelvic inflammatory disease caused by β-lactamase producing isolates of Escherichia coli.

1.4 Community-acquired Pneumonia

Community-acquired pneumonia (moderate severity only) caused by β-lactamase producing isolates of Haemophilus influenzae.

1.5 Nosocomial Pneumonia

Nosocomial pneumonia (moderate to severe) caused by β-lactamase producing isolates of Staphylococcus aureus and by piperacillin/tazobactam-susceptible Acinetobacter baumannii, Haemophilus influenzae, Klebsiella pneumoniae, and Pseudomonas aeruginosa (Nosocomial pneumonia caused by P. aeruginosa should be treated in combination with an aminoglycoside) [ see Dosage and Administration (2) ].

To reduce the development of drug-resistant bacteria and maintain the effectiveness of piperacillin and tazobactam for injection and other antibacterial drugs, piperacillin and tazobactam for injection should be used only to treat infections that are proven or strongly suspected to be caused by bacteria. When culture and susceptibility information are available, they should be considered in selecting or modifying antibacterial therapy. In the absence of such data, local epidemiology and susceptibility patterns may contribute to the empiric selection of therapy.

2 DOSAGE AND ADMINISTRATION

Piperacillin and tazobactam for injection should be administered by intravenous infusion over 30 minutes.

2.1 Adult Patients

The usual total daily dose of piperacillin and tazobactam for injection for adults is 3.375 g every six hours totaling 13.5 g (12.0 g piperacillin/1.5 g tazobactam). The usual duration of piperacillin and tazobactam for injection treatment is from 7 to 10 days.

Piperacillin and tazobactam for injection should be administered by intravenous infusion over 30 minutes.

2.2 Nosocomial Pneumonia

Initial presumptive treatment of patients with nosocomial pneumonia should start with piperacillin and tazobactam for injection at a dosage of 4.5 g every six hours plus an aminoglycoside, totaling 18.0 g (16.0 g piperacillin/2.0 g tazobactam). The recommended duration of piperacillin and tazobactam for injection treatment for nosocomial pneumonia is 7 to 14 days. Treatment with the aminoglycoside should be continued in patients from whom P. aeruginosa is isolated.

2.3 Renal Impairment

In patients with renal impairment (creatinine clearance ≤ 40 mL/min) and dialysis patients (hemodialysis and CAPD), the intravenous dose of piperacillin and tazobactam for injection should be reduced to the degree of actual renal function impairment. The recommended daily doses of piperacillin and tazobactam for injection for patients with renal impairment are as follows:

Table 1: Recommended Dosing of Piperacillin and Tazobactam for Injection in Patients with Normal Renal Function and Renal Impairment (As total grams piperacillin/tazobactam)
Renal Function
(creatinine clearance, | All Indications | Nosocomial
mL/min) | (except nosocomial pneumonia) | Pneumonia
>40 mL/min | 3.375 q6h | 4.5 q6h
20-40 mL/min* | 2.25 q6h | 3.375 q6h
<20 mL/min* | 2.25 q8h | 2.25 q6h
Hemodialysis** | 2.25 q12h | 2.25 q8h
CAPD | 2.25 q12h | 2.25 q8h
*Creatinine clearance for patients not receiving hemodialysis
**0.75 g (0.67 g piperacillin/0.08 g tazobactam) should be administered following each hemodialysis session on hemodialysis days

For patients on hemodialysis, the maximum dose is 2.25 g every twelve hours for all indications other than nosocomial pneumonia and 2.25 g every eight hours for nosocomial pneumonia. Since hemodialysis removes 30% to 40% of the administered dose, an additional dose of 0.75 g piperacillin and tazobactam for injection (0.67 g piperacillin/0.08 g tazobactam) should be administered following each dialysis period on hemodialysis days. No additional dosage of piperacillin and tazobactam for injection is necessary for CAPD patients.

2.4 Pediatric Patients

For children with appendicitis and/or peritonitis 9 months of age or older, weighing up to 40 kg, and with normal renal function, the recommended piperacillin and tazobactam for injection dosage is 100 mg piperacillin/12.5 mg tazobactam per kilogram of body weight, every 8 hours. For pediatric patients between 2 months and 9 months of age, the recommended piperacillin and tazobactam for injection dosage based on pharmacokinetic modeling, is 80 mg piperacillin/10 mg tazobactam per kilogram of body weight, every 8 hours [ see Use in Specific Populations (8.4) and Clinical Pharmacology (12.3) ]. Pediatric patients weighing over 40 kg and with normal renal function should receive the adult dose. It has not been determined how to adjust piperacillin and tazobactam for injection dosage in pediatric patients with renal impairment.

2.5 Reconstitution and Dilution of Powder Formulations

Pharmacy Bulk Package Bottles

Reconstituted stock solution must be transferred and further diluted for intravenous infusion.

The pharmacy bulk package bottle is for use in a hospital pharmacy admixture service only under a laminar flow hood. After reconstitution, entry into the vial must be made with a sterile transfer set or other sterile dispensing device, and contents should be dispensed as aliquots into intravenous solution using aseptic technique. Use entire contents of pharmacy bulk package bottle promptly. Discard unused portion after 24 hours if stored at room temperature 20°C to 25°C (68°F to 77°F), or after 48 hours if stored at refrigerated temperature 2°C to 8°C (36°F to 46°F).

Reconstitute the pharmacy bulk package bottle with exactly 152 mL of a compatible reconstitution diluent, listed below, to a concentration of 200 mg/mL of piperacillin and 25 mg/mL of tazobactam. Shake well until dissolved. Parenteral drug products should be inspected visually for particulate matter and discoloration prior to and during administration whenever solution and container permit.

Compatible Reconstitution Diluents for Pharmacy Bulk Bottles
0.9% Sodium chloride for injection
Sterile water for injection ‡
Dextrose 5%
Bacteriostatic saline/parabens
Bacteriostatic water/parabens
Bacteriostatic saline/benzyl alcohol
Bacteriostatic water/benzyl alcohol

Reconstituted piperacillin and tazobactam for injection solution should be further diluted (recommended volume per dose of 50 mL to 150 mL) in a compatible intravenous solution listed below. Administer by infusion over a period of at least 30 minutes. During the infusion it is desirable to discontinue the primary infusion solution.

Compatible Intravenous Solutions for Pharmacy Bulk Package Bottles and Single Dose Vials
0.9% Sodium chloride for injection
Sterile water for injection ‡
Dextran 6% in saline
Dextrose 5%

LACTATED RINGER’S SOLUTION IS NOT COMPATIBILE WITH PIPERACILLIN AND TAZOBACTAM FOR INJECTION.

‡ Maximum recommended volume per dose of sterile water for injection is 50 mL.

Piperacillin and tazobactam for injection should not be mixed with other drugs in a syringe or infusion bottle since compatibility has not been established.

Piperacillin and tazobactam for injection is not chemically stable in solutions that contain only sodium bicarbonate and solutions that significantly alter the pH.

Piperacillin and tazobactam for injection should not be added to blood products or albumin hydrolysates.

Parenteral drug products should be inspected visually for particulate matter or discoloration prior to administration, whenever solution and container permit.

Stability of Piperacillin and Tazobactam for Injection Powder Formulations Following Reconstitution

Piperacillin and tazobactam for injection reconstituted from pharmacy bulk package bottles is stable in glass and plastic containers (plastic syringes, I.V. bags and tubing) when used with compatible diluents. The pharmacy bulk package bottle should NOT be frozen after reconstitution. Discard unused portions after storage for 24 hours at room temperature or after storage for 48 hours at refrigerated temperature 2°C to 8°C (36°F to 46°F).

Pharmacy bulk package bottles should be used immediately after reconstitution. Discard any unused portion after 24 hours if stored at room temperature 20°C to 25°C (68°F to 77°F), or after 48 hours if stored at refrigerated temperature 2°C to 8°C (36°F to 46°F). Pharmacy bulk package bottles should not be frozen after reconstitution.

Stability studies in the I.V. bags have demonstrated chemical stability (potency, pH of reconstituted solution and clarity of solution) for up to 24 hours at room temperature and up to one week at refrigerated temperature. Piperacillin and tazobactam for injection contains no preservatives. Appropriate consideration of aseptic technique should be used.

Piperacillin and tazobactam for injection reconstituted from bulk package bottles can be used in ambulatory intravenous infusion pumps. Stability of piperacillin and tazobactam for injection in an ambulatory intravenous infusion pump has been demonstrated for a period of 12 hours at room temperature. Each dose was reconstituted and diluted to a volume of 37.5 mL or 25 mL. One-day supplies of dosing solution were aseptically transferred into the medication reservoir (I.V. bags or cartridge). The reservoir was fitted to a preprogrammed ambulatory intravenous infusion pump per the manufacturer's instructions. Stability of piperacillin and tazobactam for injection is not affected when administered using an ambulatory intravenous infusion pump.

2.6 Compatibility with Aminoglycosides

Due to the in vitro inactivation of aminoglycosides by piperacillin, piperacillin and tazobactam for injection and aminoglycosides are recommended for separate administration. Piperacillin and tazobactam for injection and aminoglycosides should be reconstituted, diluted, and administered separately when concomitant therapy with aminoglycosides is indicated [ see Drug Interactions (7.1) ].

In circumstances where co-administration via Y-site is necessary, piperacillin and tazobactam is compatible for simultaneous coadministration via Y-site infusion only with the following aminoglycosides under the following conditions:

Table 2: Compatibility with Aminoglycosides
Aminoglycoside | Piperacillin and Tazobactam Dose (grams) | Piperacillin and Tazobactam Diluent Volume (mL) | Aminoglycoside Concentration Range a (mg/mL) | Acceptable Diluents
Amikacin | 2.25, 3.375, 4.5 | 50, 100, 150 | 1.75 – 7.5 | 0.9% sodium chloride or 5% dextrose
Gentamicin | 2.25, 3.375, 4.5 | 50, 100 150 | 0.7 – 3.32 | 0.9% sodium chloride or 5% dextrose
aThe concentration ranges in Table 2 are based on administration of the aminoglycoside in divided doses (10-15 mg/kg/day in two daily doses for amikacin and 3-5 mg/kg/day in three daily doses for gentamicin). Administration of amikacin or gentamicin in a single daily dose or in doses exceeding those stated above via Y-site with piperacillin and tazobactam has not been evaluated. See package insert for each aminoglycoside for complete Dosage and Administration instructions.

Only the concentration and diluents for amikacin or gentamicin with the dosages of piperacillin and tazobactam for injection listed above have been established as compatible for coadministration via Y-site infusion. Simultaneous coadministration via Y-site infusion in any manner other than listed above may result in inactivation of the aminoglycoside by piperacillin and tazobactam.

Piperacillin and tazobactam for injection is not compatible with tobramycin for simultaneous coadministration via Y-site infusion. Compatibility of piperacillin and tazobactam with other aminoglycosides has not been established.

Parenteral drug products should be inspected visually for particulate matter and discoloration prior to administration, whenever solution and container permit.

3 DOSAGE FORMS AND STRENGTHS

Piperacillin and tazobactam for injection is supplied as a white to off-white powder in bottles of the following sizes:

Each Piperacillin and Tazobactam for Injection 40.5 g pharmacy bulk bottle contains piperacillin sodium equivalent to 36 grams of piperacillin and tazobactam sodium equivalent to 4.5 grams tazobactam.

4 CONTRAINDICATIONS

Piperacillin and tazobactam for injection is contraindicated in patients with a history of allergic reactions to any of the penicillins, cephalosporins, or β-lactamase inhibitors.

5 WARNINGS AND PRECAUTIONS

5.1 Hypersensitivity Reactions

Serious and occasionally fatal hypersensitivity (anaphylactic/anaphylactoid) reactions (including shock) have been reported in patients receiving therapy with piperacillin and tazobactam for injection. These reactions are more likely to occur in individuals with a history of penicillin, cephalosporin, or carbapenem hypersensitivity or a history of sensitivity to multiple allergens. Before initiating therapy with piperacillin and tazobactam for injection, careful inquiry should be made concerning previous hypersensitivity reactions. If an allergic reaction occurs, piperacillin and tazobactam for injection should be discontinued and appropriate therapy instituted.

5.2 Serious Skin Reactions

Serious skin reactions, such as Stevens-Johnson syndrome and toxic epidermal necrolysis, have been reported in patients receiving piperacillin and tazobactam for injection. If patients develop a skin rash they should be monitored closely and piperacillin and tazobactam for injection discontinued if lesions progress.

5.3 Clostridium difficile Associated Diarrhea

Clostridium difficile associated diarrhea (CDAD) has been reported with use of nearly all antibacterial agents, including piperacillin and tazobactam for injection, and may range in severity from mild diarrhea to fatal colitis. Treatment with antibacterial agents alters the normal flora of the colon leading to overgrowth of C. difficile.

C. difficile produces toxins A and B which contribute to the development of CDAD. Hypertoxin producing strains of C. difficile cause increased morbidity and mortality, as these infections can be refractory to antimicrobial therapy and may require colectomy. CDAD must be considered in all patients who present with diarrhea following antibacterial drug use. Careful medical history is necessary since CDAD has been reported to occur over two months after the administration of antibacterial agents.

If CDAD is suspected or confirmed, ongoing antibacterial drug use not directed against C. difficile may need to be discontinued. Appropriate fluid and electrolyte management, protein supplementation, antibacterial treatment of C. difficile, and surgical evaluation should be instituted as clinically indicated.

5.4 Hematologic Effects

Bleeding manifestations have occurred in some patients receiving β-lactam drugs, including piperacillin. These reactions have sometimes been associated with abnormalities of coagulation tests such as clotting time, platelet aggregation and prothrombin time, and are more likely to occur in patients with renal failure. If bleeding manifestations occur, piperacillin and tazobactam for injection should be discontinued and appropriate therapy instituted.

The leukopenia/neutropenia associated with piperacillin and tazobactam for injection administration appears to be reversible and most frequently associated with prolonged administration.

Periodic assessment of hematopoietic function should be performed, especially with prolonged therapy, ie, ≥ 21 days [ see Adverse Reactions (6.1) ].

5.5 Central Nervous System Effects

As with other penicillins, patients may experience neuromuscular excitability or convulsions if higher than recommended doses are given intravenously (particularly in the presence of renal failure).

5.6 Electrolyte Effects

Piperacillin and tazobactam for injection contains a total of 2.35 mEq (54 mg) of Na ^+ per gram of piperacillin in the combination product. This should be considered when treating patients requiring restricted salt intake. Periodic electrolyte determinations should be performed in patients with low potassium reserves, and the possibility of hypokalemia should be kept in mind with patients who have potentially low potassium reserves and who are receiving cytotoxic therapy or diuretics.

5.7 Development of Drug-Resistant Bacteria

Prescribing piperacillin and tazobactam for injection in the absence of a proven or strongly suspected bacterial infection is unlikely to provide benefit to the patient and increases the risk of development of drug-resistant bacteria.

6 ADVERSE REACTIONS

6.1 Clinical Trials Experience

Because clinical trials are conducted under widely varying conditions, adverse reaction rates observed in the clinical trials of a drug cannot be directly compared to rates in the clinical trials of another drug and may not reflect the rates observed in practice.

During the initial clinical investigations, 2621 patients worldwide were treated with piperacillin and tazobactam for injection in phase 3 trials. In the key North American monotherapy clinical trials (n=830 patients), 90% of the adverse events reported were mild to moderate in severity and transient in nature. However, in 3.2% of the patients treated worldwide, piperacillin and tazobactam for injection was discontinued because of adverse events primarily involving the skin (1.3%), including rash and pruritus; the gastrointestinal system (0.9%), including diarrhea, nausea, and vomiting; and allergic reactions (0.5%).

Table 3: Adverse Reactions from Piperacillin and Tazobactam for Injection
Monotherapy Clinical Trials

System Organ Class
Adverse Reaction

Gastrointestinal disorders
Diarrhea (11.3%)
Constipation (7.7%)
Nausea (6.9%)
Vomiting (3.3%)
Dyspepsia (3.3%)
Abdominal pain (1.3%)
Pseudomembranous colitis (≤1%)

General disorders and administration site conditions
Fever (2.4%)
Injection site reaction (≤1%)
Rigors (≤1%)

Immune system disorders
Anaphylaxis (≤1%)

Infections and infestations
Candidiasis (1.6%)

Metabolism and nutrition disorders
Hypoglycemia (≤1%)

Musculoskeletal and connective tissue disorders
Myalgia(≤1%)
Arthralgia (≤1%)

Nervous system disorders
Headache (7.7%)
Insomnia (6.6%)

Skin and subcutaneous tissue disorders
Rash (4.2%, including maculopapular, bullous, and urticarial)
Pruritus (3.1%)

Vascular disorders
Phlebitis (1.3%)
Thrombophlebitis (≤1%)
Hypotension (≤1%)
Purpura (≤1%)
Epistaxis (≤1%)
Flushing (≤1%)

Nosocomial Pneumonia Trials

Two trials of nosocomial lower respiratory tract infections were conducted. In one study, 222 patients were treated with piperacillin and tazobactam for injection in a dosing regimen of 4.5 g every 6 hours in combination with an aminoglycoside and 215 patients were treated with imipenem/cilastatin (500 mg/500 mg q6h) in combination with an aminoglycoside. In this trial, treatment-emergent adverse events were reported by 402 patients, 204 (91.9%) in the piperacillin/tazobactam group and 198 (92.1%) in the imipenem/cilastatin group. Twenty-five (11.0%) patients in the piperacillin/tazobactam group and 14 (6.5%) in the imipenem/cilastatin group (p > 0.05) discontinued treatment due to an adverse event.

The second trial used a dosing regimen of 3.375 g given every 4 hours with an aminoglycoside.

Table 4: Adverse Reactions from Piperacillin and Tazobactam for Injection
Plus Aminoglycoside Clinical Trials a

System Organ Class
Adverse Reaction

Blood and lymphatic system disorders
Thrombocythemia (1.4%)
Anemia (≤1%)
Thrombocytopenia (≤1%)
Eosinophilia (≤1%)

Gastrointestinal disorders
Diarrhea (20%)
Constipation (8.4%)
Nausea (5.8%)
Vomiting (2.7%)
Dyspepsia (1.9%)
Abdominal pain (1.8%)
Stomatitis (≤1%)

General disorders and administration site conditions
Fever (3.2%)
Injection site reaction (≤1%)

Infections and infestations
Oral candidiasis (3.9%)
Candidiasis (1.8%)

Investigations
BUN increased (1.8%)
Blood creatinine increased (1.8%)
Liver function test abnormal (1.4%)
Alkaline phosphatase increased (≤1%)
Aspartate aminotransferase increased (≤1%)
Alanine aminotransferase increased (≤1%)

Metabolism and nutrition disorders
Hypoglycemia (≤1%)
Hypokalemia (≤1%)

Nervous system disorders
Headache (4.5%)
Insomnia (4.5%)

Renal and urinary disorders
Renal failure (≤1%)

Skin and subcutaneous tissue disorders
Rash (3.9%)
Pruritus (3.2%)

Vascular disorders
Thrombophlebitis (1.3%)
Hypotension (1.3%)

a For adverse drug reactions that appeared in both studies the higher frequency is presented.

Pediatrics

Studies of piperacillin and tazobactam for injection in pediatric patients suggest a similar safety profile to that seen in adults. In a prospective, randomized, comparative, open-label clinical trial of pediatric patients with severe intra-abdominal infections (including appendicitis and/or peritonitis), 273 patients were treated with piperacillin and tazobactam for injection (112.5 mg/kg every 8 hours) and 269 patients were treated with cefotaxime (50 mg/kg) plus metronidazole (7.5 mg/kg) every 8 hours. In this trial, treatment-emergent adverse events were reported by 146 patients, 73 (26.7%) in the piperacillin and tazobactam for injection group and 73 (27.1%) in the cefotaxime/metronidazole group. Six patients (2.2%) in the piperacillin and tazobactam for injection group and 5 patients (1.9%) in the cefotaxime/metronidazole group discontinued due to an adverse event.

Adverse Laboratory Events (Seen During Clinical Trials)

Of the trials reported, including that of nosocomial lower respiratory tract infections in which a higher dose of piperacillin and tazobactam for injection was used in combination with an aminoglycoside, changes in laboratory parameters include:

Hematologic—decreases in hemoglobin and hematocrit, thrombocytopenia, increases in platelet count, eosinophilia, leukopenia, neutropenia. These patients were withdrawn from therapy; some had accompanying systemic symptoms (e.g., fever, rigors, chills).

Coagulation—positive direct Coombs' test, prolonged prothrombin time, prolonged partial thromboplastin time

Hepatic—transient elevations of AST (SGOT), ALT (SGPT), alkaline phosphatase, bilirubin

Renal—increases in serum creatinine, blood urea nitrogen

Additional laboratory events include abnormalities in electrolytes (i.e., increases and decreases in sodium, potassium, and calcium), hyperglycemia, decreases in total protein or albumin, blood glucose decreased, gamma-glutamyltransferase increased, hypokalemia, and bleeding time prolonged.

6.2 Post-Marketing Experience

In addition to the adverse drug reactions identified in clinical trials in Table 3 and Table 4, the following adverse reactions have been identified during postapproval use of piperacillin and tazobactam for injection.

Because these reactions are reported voluntarily from a population of uncertain size, it is not always possible to reliably estimate their frequency or establish causal relationship to drug exposure.

Gastrointestinal—hepatitis, jaundice

Hematologic—hemolytic anemia, agranulocytosis, pancytopenia

Immune—hypersensitivity reactions, anaphylactic/anaphylactoid reactions (including shock)

Renal—interstitial nephritis

Skin and Appendages—erythema multiforme, Stevens-Johnson syndrome, toxic epidermal necrolysis

6.3 Additional Experience with piperacillin

The following adverse reaction has also been reported for piperacillin for injection:

Skeletal—prolonged muscle relaxation [ see Drug Interactions (7.4)].

Post-marketing experience with piperacillin and tazobactam for injection in pediatric patients suggests a similar safety profile to that seen in adults.

7 DRUG INTERACTIONS

7.1 Aminoglycosides

Piperacillin may inactivate aminoglycosides by converting them to microbiologically inert amides.

In vivo inactivation : When aminoglycosides are administered in conjunction with piperacillin to patients with end-stage renal disease requiring hemodialysis, the concentrations of the aminoglycosides (especially tobramycin) may be significantly reduced and should be monitored.

Sequential administration of piperacillin and tazobactam for injection and tobramycin to patients with either normal renal function or mild to moderate renal impairment has been shown to modestly decrease serum concentrations of tobramycin but no dosage adjustment is considered necessary.

In vitro inactivation:

Due to the in vitro inactivation of aminoglycosides by piperacillin, piperacillin and tazobactam for injection and aminoglycosides are recommended for separate administration. Piperacillin and tazobactam for injection and aminoglycosides should be reconstituted, diluted, and administered separately when concomitant therapy with aminoglycosides is indicated. Piperacillin and tazobactam for injection is compatible with amikacin and gentamicin for simultaneous Y-site infusion in certain diluents and at specific concentrations. Piperacillin and tazobactam for injection is not compatible with tobramycin for simultaneous Y-site infusion [ see Dosage and Administration (2.6) ].

7.2 Probenecid

Probenecid administered concomitantly with piperacillin and tazobactam prolongs the half-life of piperacillin by 21% and that of tazobactam by 71% because probenecid inhibits tubular renal secretion of both piperacillin and tazobactam. Probenecid should not be co-administered with piperacillin and tazobactam for injection unless the benefit outweighs the risk.

7.3 Anticoagulants

Coagulation parameters should be tested more frequently and monitored regularly during simultaneous administration of high doses of heparin, oral anticoagulants, or other drugs that may affect the blood coagulation system or the thrombocyte function. [ see Warnings and Precautions (5.4) ]

7.4 Vecuronium

Piperacillin when used concomitantly with vecuronium has been implicated in the prolongation of the neuromuscular blockade of vecuronium. Piperacillin and tazobactam for injection could produce the same phenomenon if given along with vecuronium. Due to their similar mechanism of action, it is expected that the neuromuscular blockade produced by any of the non-depolarizing muscle relaxants could be prolonged in the presence of piperacillin. Monitor for adverse reactions related to neuromuscular blockade (See package insert for vecuronium bromide).

7.5 Methotrexate

Limited data suggests that co-administration of methotrexate and piperacillin may reduce the clearance of methotrexate due to competition for renal secretion. The impact of tazobactam on the elimination of methotrexate has not been evaluated. If concurrent therapy is necessary, serum concentrations of methotrexate as well as the signs and symptoms of methotrexate toxicity should be frequently monitored.

7.6 Effects on Laboratory Tests

There have been reports of positive test results using the Bio-Rad Laboratories Platelia Aspergillus EIA test in patients receiving piperacillin/tazobactam injection who were subsequently found to be free of Aspergillus infection. Cross-reactions with non- Aspergillus polysaccharides and polyfuranoses with the Bio-Rad Laboratories Platelia Aspergillus EIA test have been reported. Therefore, positive test results in patients receiving piperacillin/tazobactam should be interpreted cautiously and confirmed by other diagnostic methods.

As with other penicillins, the administration of piperacillin and tazobactam for injection may result in a false-positive reaction for glucose in the urine using a copper-reduction method (CLINITEST ®). It is recommended that glucose tests based on enzymatic glucose oxidase reactions be used.

8 USE IN SPECIFIC POPULATIONS

8.1 Pregnancy

Teratogenic effects—Pregnancy Category B

Piperacillin/tazobactam

Teratology studies have been performed in mice and rats and have revealed no evidence of harm to the fetus when piperacillin/tazobactam is administered intravenously up to a dose of 3000/750 mg/kg piperacillin/tazobactam which is 1 to 2 times and 2 to 3 times the human dose of piperacillin and tazobactam, respectively, based on body-surface area (mg/m ^2).

Piperacillin and tazobactam cross the placenta in humans.

There are, however, no adequate and well-controlled studies with the piperacillin/tazobactam combination or with piperacillin or tazobactam alone in pregnant women. Because animal reproduction studies are not always predictive of the human response, this drug should be used during pregnancy only if clearly needed.

8.3 Nursing Mothers

Piperacillin is excreted in low concentrations in human milk; tazobactam concentrations in human milk have not been studied. Caution should be exercised when piperacillin and tazobactam for injection is administered to a nursing woman.

8.4 Pediatric Use

Use of piperacillin and tazobactam for injection in pediatric patients 2 months of age or older with appendicitis and/or peritonitis is supported by evidence from well-controlled studies and pharmacokinetic studies in adults and in pediatric patients. This includes a prospective, randomized, comparative, open-label clinical trial with 542 pediatric patients 2-12 years of age with complicated intra-abdominal infections, in which 273 pediatric patients received piperacillin/tazobactam. Safety and efficacy in pediatric patients less than 2 months of age have not been established [ see Clinical Pharmacology (12) and Dosage and Administration (2) ].

It has not been determined how to adjust piperacillin and tazobactam for injection dosage in pediatric patients with renal impairment.

8.5 Geriatric Use

Patients over 65 years are not at an increased risk of developing adverse effects solely because of age. However, dosage should be adjusted in the presence of renal impairment [ see Dosage and Administration (2) ].

In general, dose selection for an elderly patient should be cautious, usually starting at the low end of the dosing range, reflecting the greater frequency of decreased hepatic, renal, or cardiac function, and of concomitant disease or other drug therapy.

Piperacillin and tazobactam for injection contains 54 mg (2.35 mEq) of sodium per gram of piperacillin in the combination product. At the usual recommended doses, patients would receive between 648 and 864 mg/day (28.2 and 37.6 mEq) of sodium. The geriatric population may respond with a blunted natriuresis to salt loading. This may be clinically important with regard to such diseases as congestive heart failure.

This drug is known to be substantially excreted by the kidney, and the risk of toxic reactions to this drug may be greater in patients with impaired renal function. Because elderly patients are more likely to have decreased renal function, care should be taken in dose selection, and it may be useful to monitor renal function.

8.6 Renal Impairment

In patients with creatinine clearance ≤ 40 mL/min and dialysis patients (hemodialysis and CAPD), the intravenous dose of piperacillin and tazobactam for injection should be reduced to the degree of renal function impairment [ see Dosage and Administration (2) ].

8.7 Hepatic Impairment

Dosage adjustment of piperacillin and tazobactam for injection is not warranted in patients with hepatic cirrhosis [See Clinical Pharmacology (12.3)].

8.8 Patients with Cystic Fibrosis

As with other semisynthetic penicillins, piperacillin therapy has been associated with an increased incidence of fever and rash in cystic fibrosis patients.

10 OVERDOSAGE

There have been postmarketing reports of overdose with piperacillin/tazobactam. The majority of those events experienced, including nausea, vomiting, and diarrhea, have also been reported with the usual recommended dosages. Patients may experience neuromuscular excitability or convulsions if higher than recommended doses are given intravenously (particularly in the presence of renal failure) [ see Warnings and Precautions (5.5) ].

Treatment should be supportive and symptomatic according the patient's clinical presentation. Excessive serum concentrations of either piperacillin or tazobactam may be reduced by hemodialysis. Following a single 3.375 g dose of piperacillin/tazobactam, the percentage of the piperacillin and tazobactam dose removed by hemodialysis was approximately 31% and 39%, respectively [ see Clinical Pharmacology (12) ].

11 DESCRIPTION

Piperacillin and tazobactam for injection is an injectable antibacterial combination product consisting of the semisynthetic antibacterial piperacillin sodium and the β-lactamase inhibitor tazobactam sodium for intravenous administration.

Piperacillin sodium is derived from D(-)-α-aminobenzyl-penicillin. The chemical name of piperacillin sodium is sodium (2 S,5 R,6 R)-6-[(R)-2-(4-ethyl-2,3-dioxo-1-piperazinecarboxamido)-2-phenylacetamido]-3,3-dimethyl-7-oxo-4-thia-1-azabicyclo[3.2.0]heptane-2-carboxylate. The chemical formula is C 23H 26N 5NaO 7S and the molecular weight is 539.5. The chemical structure of piperacillin sodium is:

Tazobactam sodium, a derivative of the penicillin nucleus, is a penicillanic acid sulfone. Its chemical name is sodium (2 S,3 S,5 R)-3-methyl-7-oxo-3-(1 H-1,2,3-triazol-1-ylmethyl)-4-thia-1-azabicyclo[3.2.0]heptane-2-carboxylate-4,4-dioxide. The chemical formula is C 10H 11N 4NaO 5S and the molecular weight is 322.3. The chemical structure of tazobactam sodium is:

Piperacillin and tazobactam for injection, piperacillin/tazobactam parenteral combination, is a white to off-white sterile, cryodesiccated powder consisting of piperacillin and tazobactam as their sodium salts packaged in glass bottles. The product does not contain excipients or preservatives.

The pharmacy bulk package bottle is a container of sterile preparation which contains many single doses for parenteral use. The contents are intended for use in a pharmacy admixture program and are restricted to the preparation of admixtures for intravenous infusion.

Each piperacillin and tazobactam for injection 40.5 g pharmacy bulk package bottle contains piperacillin sodium equivalent to 36 grams of piperacillin and tazobactam sodium equivalent to 4.5 g of tazobactam sufficient for delivery of multiple doses.

Piperacillin and tazobactam for injection is a monosodium salt of piperacillin and a monosodium salt of tazobactam containing a total of 2.35 mEq (54 mg) of sodium (Na ^+) per gram of piperacillin in the combination product.

12 CLINICAL PHARMACOLOGY

12.1 Mechanism of Action

Piperacillin and tazobactam for injection is an antibacterial drug [ see Microbiology (12.4) ].

12.2 Pharmacodynamics

The pharmacodynamic parameter for piperacillin/tazobactam that is most predictive of clinical and microbiological efficacy is time above MIC.

12.3 Pharmacokinetics

The mean and coefficients of variation (CV%) for the pharmacokinetic parameters of piperacillin and tazobactam after multiple intravenous doses are summarized in Table 5.

Table 5: Mean (CV%) Piperacillin and Tazobactam PK Parameters Piperacillin
Piperacillin
Piperacillin/Tazobactam Dose a | C max mcg/mL | AUC b mcg•h/mL | CL mL/min | V L | T 1/2 h | CL R mL/min
2.25 g | 134 | 131 (14) | 257 | 17.4 | 0.79 | -
3.375 g | 242 | 242 (10) | 207 | 15.1 | 0.84 | 140
4.5 g | 298 | 322 (16) | 210 | 15.4 | 0.84 | -
Tazobactam
Piperacillin/Tazobactam Dose a | C max mcg/mL | AUC b mcg•h/mL | CL mL/min | V L | T 1/2 h | CL R mL/min
2.25 g | 15 | 16.0 (21) | 258 | 17.0 | 0.77 | -
3.375 g | 24 | 25.0 (8) | 251 | 14.8 | 0.68 | 166
4.5 g | 34 | 39.8 (15) | 206 | 14.7 | 0.82 | -
aPiperacillin and tazobactam were given in combination, infused over 30 minutes.
bNumbers in parentheses are coefficients of variation (CV%).

Peak plasma concentrations of piperacillin and tazobactam are attained immediately after completion of an intravenous infusion of piperacillin and tazobactam for injection. Piperacillin plasma concentrations, following a 30-minute infusion of piperacillin and tazobactam for injection, were similar to those attained when equivalent doses of piperacillin were administered alone. Steady-state plasma concentrations of piperacillin and tazobactam were similar to those attained after the first dose due to the short half-lives of piperacillin and tazobactam.

Distribution

Both piperacillin and tazobactam are approximately 30% bound to plasma proteins. The protein binding of either piperacillin or tazobactam is unaffected by the presence of the other compound. Protein binding of the tazobactam metabolite is negligible.

Piperacillin and tazobactam are widely distributed into tissues and body fluids including intestinal mucosa, gallbladder, lung, female reproductive tissues (uterus, ovary, and fallopian tube), interstitial fluid, and bile. Mean tissue concentrations are generally 50% to 100% of those in plasma. Distribution of piperacillin and tazobactam into cerebrospinal fluid is low in subjects with non-inflamed meninges, as with other penicillins (see Table 6).

Table 6: Piperacillin/Tazobactam Concentrations in Selected Tissues and Fluids after
Single 4 g/0.5 g 30-min IV Infusion of Piperacillin and Tazobactam for Injection
Tissue or Fluid | N a | Sampling period b (h) | Mean PIP Concentration Range (mg/L) | Tissue:Plasma Range | Tazo Concentration Range (mg/L) | Tazo Tissue:Plasma Range
Skin | 35 | 0.5 – 4.5 | 34.8 – 94.2 | 0.60 – 1.1 | 4.0 – 7.7 | 0.49 – 0.93
Fatty Tissue | 37 | 0.5 – 4.5 | 4.0 – 10.1 | 0.097 – 0.115 | 0.7 – 1.5 | 0.10 – 0.13
Muscle | 36 | 0.5 – 4.5 | 9.4 – 23.3 | 0.29 – 0.18 | 1.4 - 2.7 | 0.18 – 0.30
Proximal Intestinal Mucosa | 7 | 1.5 – 2.5 | 31.4 | 0.55 | 10.3 | 1.15
Distal Intestinal Mucosa | 7 | 1.5 – 2.5 | 31.2 | 0.59 | 14.5 | 2.1
Appendix | 22 | 0.5 – 2.5 | 26.5 – 64.1 | 0.43 – 0.53 | 9.1 – 18.6 | 0.80 – 1.35
a Each subject provided a single sample.
b Time from the start of the infusion

Metabolism

Piperacillin is metabolized to a minor microbiologically active desethyl metabolite. Tazobactam is metabolized to a single metabolite that lacks pharmacological and antibacterial activities.

Excretion

Following single or multiple piperacillin and tazobactam for injection doses to healthy subjects, the plasma half-life of piperacillin and of tazobactam ranged from 0.7 to 1.2 hours and was unaffected by dose or duration of infusion.

Both piperacillin and tazobactam are eliminated via the kidney by glomerular filtration and tubular secretion. Piperacillin is excreted rapidly as unchanged drug with 68% of the administered dose excreted in the urine. Tazobactam and its metabolite are eliminated primarily by renal excretion with 80% of the administered dose excreted as unchanged drug and the remainder as the single metabolite. Piperacillin, tazobactam and desethyl piperacillin are also secreted into the bile.

Specific Populations

Renal impairment

After the administration of single doses of piperacillin/tazobactam to subjects with renal impairment, the half-life of piperacillin and of tazobactam increases with decreasing creatinine clearance. At creatinine clearance below 20 mL/min, the increase in half-life is twofold for piperacillin and fourfold for tazobactam compared to subjects with normal renal function. Dosage adjustments for piperacillin and tazobactam for injection are recommended when creatinine clearance is below 40 mL/min in patients receiving the usual recommended daily dose of piperacillin and tazobactam for injection. See Dosage and Administration (2) for specific recommendations for the treatment of patients with renal impairment.

Hemodialysis removes 30% to 40% of a piperacillin/tazobactam dose with an additional 5% of the tazobactam dose removed as the tazobactam metabolite. Peritoneal dialysis removes approximately 6% and 21% of the piperacillin and tazobactam doses, respectively, with up to 16% of the tazobactam dose removed as the tazobactam metabolite. For dosage recommendations for patients undergoing hemodialysis [ see Dosage and Administration (2) .]

Hepatic Impairment

The half-life of piperacillin and of tazobactam increases by approximately 25% and 18%, respectively, in patients with hepatic cirrhosis compared to healthy subjects. However, this difference does not warrant dosage adjustment of piperacillin and tazobactam for injection due to hepatic cirrhosis.

Pediatrics

Piperacillin and tazobactam pharmacokinetics were studied in pediatric patients 2 months of age and older. The clearance of both compounds is slower in the younger patients compared to older children and adults.

In a population PK analysis, estimated clearance for 9 month-old to 12 year-old patients was comparable to adults, with a population mean (SE) value of 5.64 (0.34) mL/min/kg. The piperacillin clearance estimate is 80% of this value for pediatric patients 2-9 months old. In patients younger than 2 months of age, clearance of piperacillin is slower compared to older children; however, it is not adequately characterized for dosing recommendations. The population mean (SE) for piperacillin distribution volume is 0.243 (0.011) L/kg and is independent of age.

Geriatrics

The impact of age on the pharmacokinetics of piperacillin and tazobactam was evaluated in healthy male subjects, aged 18-35 years (n=6) and aged 65 to 80 years (n=12). Mean half-life for piperacilln and tazobactam was 32% and 55% higher, respectively, in the elderly compared to the younger subjects. This difference may be due to age-related changes in creatinine clearance.

Race

The effect of race on piperacillin and tazobactam was evaluated in healthy male volunteers. No difference in piperacillin or tazobactam pharmacokinetics was observed between Asian (n=9) and Caucasian (n=9) healthy volunteers who received single 4/0.5 g doses.

Drug Interactions

The potential for pharmacokinetic drug interactions between piperacillin and tazobactam for injection and aminoglycosides, probenecid, vancomycin, heparin, vecuronium, and methotrexate has been evaluated [ see Drug Interactions (7) ].

12.4 Microbiology

Mechanism of Action

Piperacillin sodium exerts bactericidal activity by inhibiting septum formation and cell wall synthesis of susceptible bacteria. In vitro, piperacillin is active against a variety of Gram-positive and Gram-negative aerobic and anaerobic bacteria. Tazobactam sodium has little clinically relevant in vitro activity against bacteria due to its reduced affinity to penicillin-binding proteins. It is, however, a β-lactamase inhibitor of the Molecular class A enzymes, including Richmond-Sykes class III (Bush class 2b & 2b') penicillinases and cephalosporinases. It varies in its ability to inhibit class II and IV (2a & 4) penicillinases. Tazobactam does not induce chromosomally-mediated β-lactamases at tazobactam concentrations achieved with the recommended dosage regimen.

Spectrum of Activity

Piperacillin/tazobactam has been shown to be active against most isolates of the following microorganisms both in vitro and in clinical infections [ see Indications and Usage (1) ].

Gram-positive bacteria:

Staphylococcus aureus (methicillin susceptible isolates only)

Gram-negative bacteria:
Acinetobacter baumannii
Escherichia coli
Haemophilus influenzae (excluding β-lactamase negative, ampicillin-resistant isolates)
Klebsiella pneumoniae
Pseudomonas aeruginosa (given in combination with an aminoglycoside to which the isolate is susceptible)

Anaerobic bacteria:
Bacteroides fragilis group (B. fragilis, B. ovatus, B. thetaiotaomicron, and B. vulgatus)

The following in vitro data are available, but their clinical significance is unknown.

At least 90% of the following microorganisms exhibit an in vitro minimum inhibitory concentration (MIC) less than or equal to the susceptible breakpoint for piperacillin/tazobactam. However, the safety and effectiveness of piperacillin/tazobactam in treating clinical infections due to these bacteria have not been established in adequate and well-controlled clinical trials.

Gram-positive bacteria:
Enterococcus faecalis (ampicillin or penicillin-susceptible isolates only) Staphylococcus epidermidis (methicillin susceptible isolates only)
Streptococcus agalactiae†
Streptococcus pneumoniae† (penicillin-susceptible isolates only)
Streptococcus pyogenes†
Viridans group streptococci †

Gram-negative bacteria:
Citrobacter koseri
Moraxella catarrhalis
Morganella morganii
Neisseria gonorrhoeae
Proteus mirabilis
Proteus vulgaris
Serratia marcescens
Providencia stuartii
Providencia rettgeri
Salmonella enterica

Anaerobic bacteria:
Clostridium perfringens
Bacteroides distasonis
Prevotella melaninogenica

†These are not β-lactamase producing bacteria and, therefore, are susceptible to piperacillin alone.

Susceptibility Testing Methods

As is recommended with all antimicrobials, the results of in vitro susceptibility tests, when available, should be provided to the physician as periodic reports, which describe the susceptibility profile of nosocomial and community-acquired pathogens. These reports should aid the physician in selecting the most effective antimicrobial.

Dilution Techniques:

Quantitative methods are used to determine antimicrobial minimum inhibitory concentrations (MICs). These MICs provide estimates of the susceptibility of bacteria to antimicrobial compounds. The MICs should be determined using a standardized procedure. Standardized procedures are based on a dilution method (broth or agar) or equivalent with standardized inoculum concentrations and standardized concentrations of piperacillin and tazobactam powders. ^1,2 MIC values should be determined using serial dilutions of piperacillin combined with a fixed concentration of 4 mcg/mL tazobactam. The MIC values obtained should be interpreted according to criteria provided in Table 7.

Diffusion Technique:

Quantitative methods that require measurement of zone diameters also provide reproducible estimates of the susceptibility of bacteria to antimicrobial compounds. The zone size provides an estimate of the susceptibility of bacteria to antimicrobial compounds. The zone size should be determined using a standardized test method ^1,3 and requires the use of standardized inoculum concentrations. This procedure uses paper disks impregnated with 100 mcg of piperacillin and 10 mcg of tazobactam to test the susceptibility of microorganisms to piperacillin/tazobactam. The disk diffusion interpreted criteria are provided in Table 7.

Anaerobic Techniques

For anaerobic bacteria, the susceptibility to piperacillin/tazobactam can be determined by the reference agar dilution method. ^4

Table 7: Susceptibility Interpretive Criteria for Piperacillin/Tazobactam
 | Susceptibility Test Result Interpretive Criteria
 | Minimal Inhibitory Concentration (MIC in mcg/mL) |  |  | Disk Diffusion (Zone Diameter in mm)
Pathogen | S | I | R | S | I | R
Enterobacteriaceae | ≤ 16 | 32 – 64 | ≥ 128 | ≥ 21 | 18 – 20 | ≤ 17
Acinetobacter baumannii | ≤ 16 | 32 – 64 | ≥ 128 | ≥ 21 | 18 – 20 | ≤ 17
Haemophilus influenzae a | ≤ 1 | - | ≥ 2 | ≥ 21 | - | -
Pseudomonas aeruginosa | ≤ 16 | 32 – 64 | ≥ 128 | ≥ 21 | 15 – 20 | ≤ 14
Bacteroides fragilis group | ≤ 32 | 64 | ≥ 128 | - | - | -
aThese interpretive criteria for Haemophilus influenzae are applicable only to tests performed using Haemophilus Test Medium inoculated with a direct colony suspension and incubated at 35°C in ambient air for 20 to 24 hours. Note: Susceptibility of staphylococci to piperacillin/tazobactam may be deduced from testing only penicillin and either cefoxitin or oxacillin.

A report of S (“Susceptible”) indicates that the pathogen is likely to be inhibited if the antimicrobial compound in the blood reaches the concentration at the infection site necessary to inhibit growth of the pathogen. A report of I (“Intermediate”) indicates that the results should be considered equivocal, and if the microorganism is not fully susceptible to alternative, clinically feasible drugs, the test should be repeated. This category implies possible clinical applicability in body sites where the drug is physiologically concentrated or in situations where high dosage of drug can be used. This category also provides a buffer zone, which prevents small, uncontrolled technical factors from causing major discrepancies in interpretation. A report of R (“Resistant”) indicates that the pathogen is not likely to be inhibited even if the antimicrobial compound in the blood reaches the concentration usually achievable at the infection site; other therapy should be considered.

Quality Control

Standardized susceptibility test procedures require the use of quality controls to monitor and ensure the accuracy and precision of supplies and reagents used in the assay, and the techniques of the individuals performing the test procedures. ^1,2,3,4 Standard piperacillin/tazobactam powder should provide the following ranges of values noted in Table 8 . Quality control bacteria are specific strains of bacteria with intrinsic biological properties relating to resistance mechanisms and their genetic expression within the microorganism; the specific strains used for microbiological quality control are not clinically significant.

Table 8: Acceptable Quality Control Ranges for Piperacillin/Tazobactam
to Be Used in Validation of Susceptibility Test
 | Acceptable Quality Control Ranges
 | Minimum Inhibitory
 | Concentration | Disk Diffusion
QC Strain | Range (MIC in mcg/mL) | Zone Diameter Ranges in mm
Escherichia coli ATCC 25922 | 1 – 4 | 24 – 30
Escherichia coli ATCC 35218 | 0.5 – 2 | 24 – 30
Pseudomonas aeruginosa ATCC 27853 | 1 – 8 | 25 – 33
Haemophilus influenzaea ATCC 49247 | 0.06 – 0.5 | 33 – 38
Staphylococcus aureus ATCC 29213 | 0.25 – 2 | -
Staphylococcus aureus ATCC 25923 | - | 27 – 36
Bacteroides fragilisb ATCC 25285 | 0.12 – 0.5 | -
Bacteroides thetaiotaomicronb ATCC 29741 | 4 – 16 | -
Clostridium difficileb ATCC 700057 | 4 – 16 | -
Eubacterium lentumb ATCC 43055 | 4 – 16 | -
a This quality control range for Haemophilus influenzae is applicable only to tests performed using Haemophilus Test Medium inoculated with a direct colony suspension and incubated at 35°C in ambient air for 20 to 24 hours.
b The quality control ranges for Bacteroides fragilis and Bacteroides thetaiotaomicron are applicable only to tests performed using the agar dilution method.

13 NONCLINICAL TOXICOLOGY

13.1 Carcinogenesis, Mutagenesis, Impairment of Fertility

Long-term carcinogenicity studies in animals have not been conducted with piperacillin/tazobactam, piperacillin, or tazobactam.

Piperacillin/Tazobactam

Piperacillin/tazobactam was negative in microbial mutagenicity assays, the unscheduled DNA synthesis (UDS) test, a mammalian point mutation (Chinese hamster ovary cell HPRT) assay, and a mammalian cell (BALB/c-3T3) transformation assay. In vivo, piperacillin/tazobactam did not induce chromosomal aberrations in rats.

Piperacillin/tazobactam

Reproduction studies have been performed in rats and have revealed no evidence of impaired fertility when piperacillin/tazobactam is administered intravenously up to a dose of 1280/320 mg/kg piperacillin/tazobactam, which is similar to the maximum recommended human daily dose based on body-surface area (mg/m ^2).

15 REFERENCES

- Clinical and Laboratory Standards Institute (CLSI). Performance Standards for Antimicrobial Susceptibility Testing; Twenty-third Informational Supplement. CLSI document M100-S23, Clinical and Laboratory Standards Institute, 950 West Valley Road, Suite 2500, Wayne, Pennsylvania 19087, USA, 2013.
- Clinical and Laboratory Standards Institute (CLSI). Methods for Dilution Antimicrobial Susceptibility Tests for Bacteria that Grow Aerobically; Approved Standard – Ninth Edition. CLSI document M07-A9, Clinical and Laboratory Standards Institute, 950 West Valley Road, Suite 2500, Wayne, Pennsylvania 19087, USA, 2012.
- Clinical and Laboratory Standards Institute (CLSI). Performance Standards for Antimicrobial Disk Diffusion Susceptibility Tests; Approved Standard – Eleventh Edition. CLSI document M02-A11, Clinical and Laboratory Standards Institute, 950 West Valley Road, Suite 2500, Wayne, Pennsylvania 19087, USA, 2012.
- Clinical and Laboratory Standards Institute (CLSI). Methods for Antimicrobial Susceptibility Testing of Anaerobic Bacteria; Approved Standard – Eight Edition. CLSI document M11-A8. Clinical and Laboratory Standards Institute, 950 West Valley Road, Suite 2500, Wayne, PA 19087 USA, 2012.

CLINITEST ®is a registered trademark of Siemens Healthcare Diagnostics Inc.

16 HOW SUPPLIED/STORAGE AND HANDLING

Piperacillin and Tazobactam for Injection is supplied in the following size:

- Each Piperacillin and Tazobactam for Injection 40.5 g pharmacy bulk package bottle provides piperacillin sodium equivalent to 36 grams of piperacillin and tazobactam sodium equivalent to 4.5 g of tazobactam. Each pharmacy bulk package bottle contains 84.6 mEq (1945 mg) of sodium.

Product Code NP304074, NDC 63323-304-78

Piperacillin and Tazobactam for Injection pharmacy bulk package bottles should be stored at 20°C to 25°C (68°F to 77°F) [see USP Controlled Room Temperature] prior to reconstitution.

This container closure is not made with natural rubber latex.

17 PATIENT COUNSELING INFORMATION

Patients should be counseled that antibacterial drugs including piperacillin and tazobactam for injection should only be used to treat bacterial infections. They do not treat viral infections (e.g., the common cold). When piperacillin and tazobactam for injection is prescribed to treat a bacterial infection, patients should be told that although it is common to feel better early in the course of therapy, the medication should be taken exactly as directed. Skipping doses or not completing the full course of therapy may (1) decrease the effectiveness of the immediate treatment and (2) increase the likelihood that bacteria will develop resistance and will not be treatable by piperacillin and tazobactam for injection or other antibacterial drugs in the future.

Diarrhea is a common problem caused by antibacterial drugs which usually ends when the drug is discontinued. Sometimes after starting treatment with antibacterial drugs, patients can develop watery and bloody stools (with or without stomach cramps and fever) even as late as two or more months after having taken the last dose of the drug. If this occurs, patients should contact their physician as soon as possible.

For all questions concerning adverse reactions associated with the use of this product or for inquiries concerning our products, please contact us at 1-800-551-7176 or WWW.FRESENIUS-KABI.US.

NOVAPLUS is a registered trademark of Novation, LLC.

Manufactured for:
Fresenius Kabi USA, LLC

Lake Zurich, IL 60047 Made in Italy
451443 855993/Issued: April 2015

PRINCIPAL DISPLAY PANEL

Piperacillin and Tazobactam 40.5 grams per Pharmacy Bulk Package Bottle Label
NDC 63323-304-78
855992
PIPERACILLIN AND TAZOBACTAM FOR INJECTION
Pharmacy Bulk Package- Not for Direct Infusion
Reconstituted stock solution must be transferred and further diluted for IV infusion.
40.5 grams per Pharmacy Bulk Package
For Intravenous Use Only
Rx only